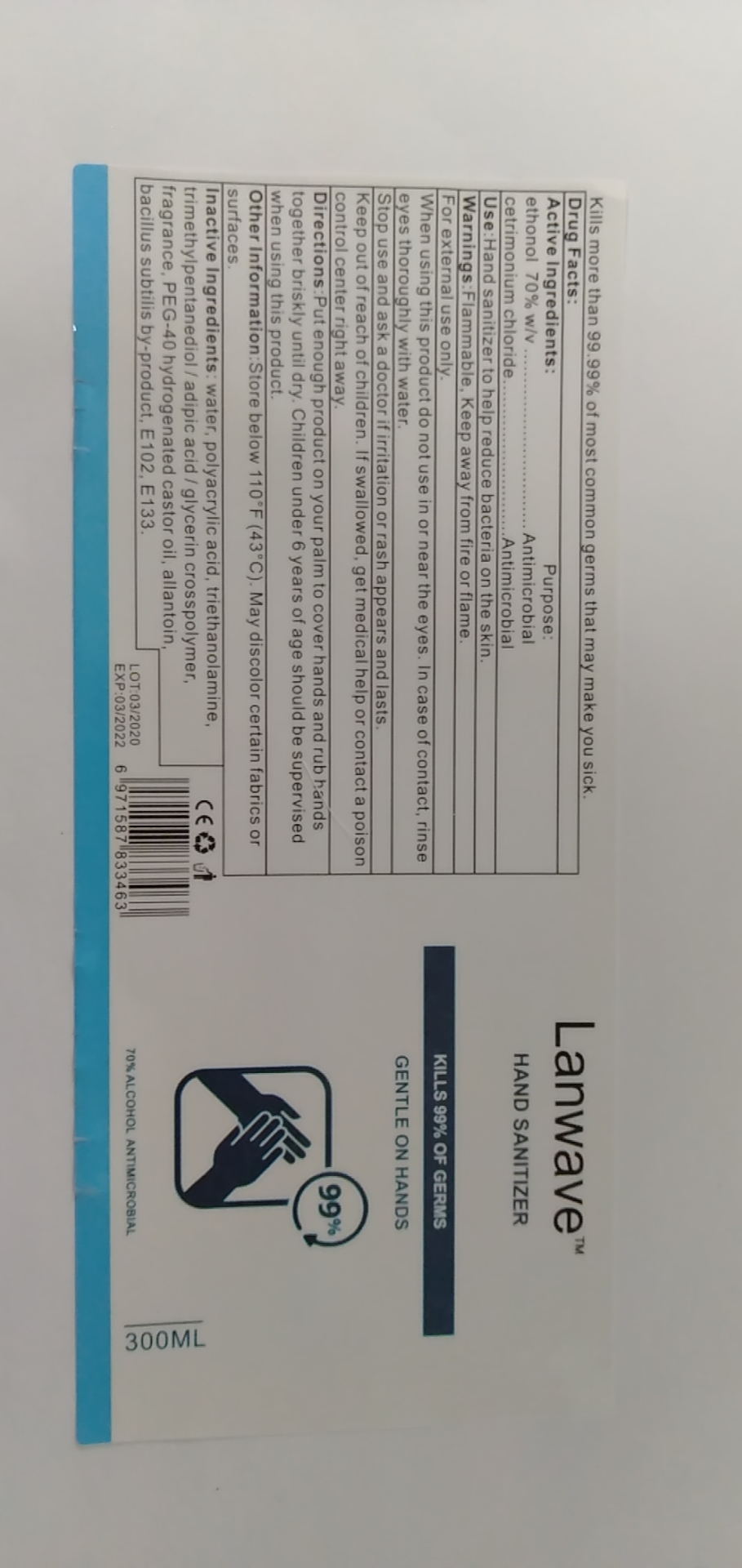 DRUG LABEL: Lamwave antimicrobial hand sanitizers gel
NDC: 41878-001 | Form: GEL
Manufacturer: Guangzhou Youmei Biotechnology Co., Ltd.
Category: otc | Type: HUMAN OTC DRUG LABEL
Date: 20200416

ACTIVE INGREDIENTS: BACILLUS AMYLOLIQUEFACIENS 0.03 mg/60 mL; ALLANTOIN 0.03 mg/60 mL
INACTIVE INGREDIENTS: WATER; ALCOHOL; TRIMETHYL-1,3-PENTANEDIOL; TRIETHYLAMINE; CARBOMER HOMOPOLYMER, UNSPECIFIED TYPE

DOSAGE AND ADMINISTRATION

Store below 110°F(43°C). May discolor certain fabrics or surfaces.

INACTIVE INGREDIENT

ethanol

pure water

Carbomer

trimethylpentylenediol / adipic acid / glycerine crosslinked aggregate

triethylamine

PURPOSE

Disinfection
Sterilization

INDICATIONS AND USAGE

Put enough product on your palm to cover hands and rub hands together briskly until dry.

ACTIVE INGREDIENT

allantoin

Fermentation products of bacillus

keep out of children

WARNINGS

1.Flammable, Keep away from fire or flame。

2.For external use only When using this product do not use in or near the eyes. In case of contact, rinse eyes thoroughly with water.

3.Stop use and ask a doctor if irritation or rash appears and lasts.

4.Keep out of reach of children. If swallowed，get medical help or contact a poison control center right away.